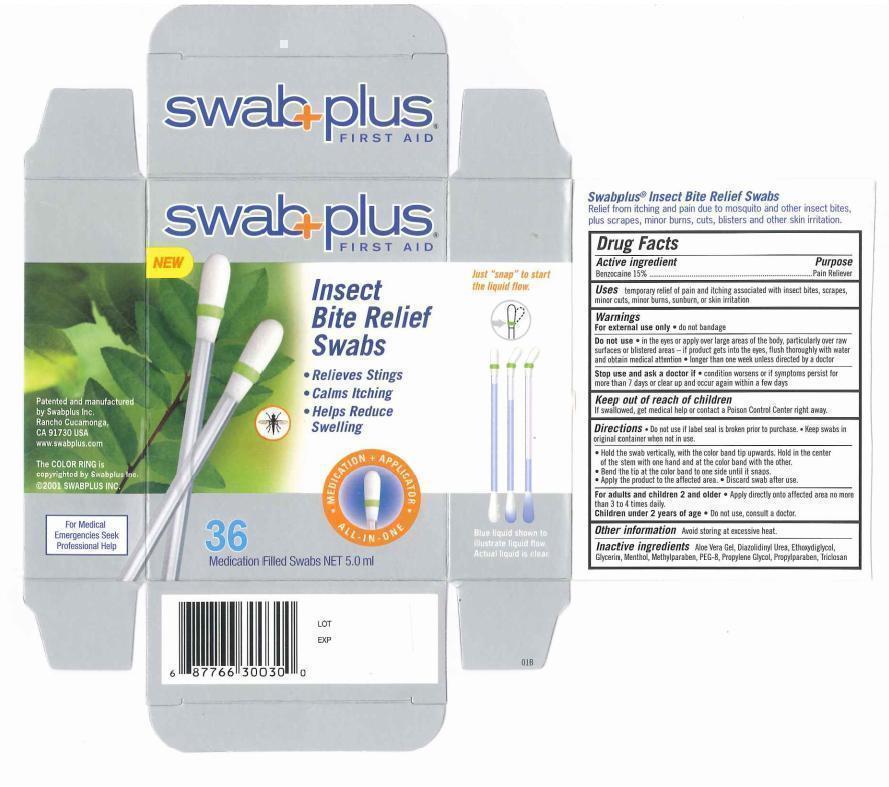 DRUG LABEL: Insect Bite Relief
NDC: 65734-300 | Form: SOLUTION
Manufacturer: Swabplus Inc.
Category: otc | Type: HUMAN OTC DRUG LABEL
Date: 20130412

ACTIVE INGREDIENTS: Benzocaine 150 mg/1 mL
INACTIVE INGREDIENTS: Polyethylene Glycol 400; DIETHYLENE GLYCOL MONOETHYL ETHER; Glycerin; PROPYLENE GLYCOL; ALOE VERA LEAF; Triclosan; Menthol

Insect Bite Relief Swabs

Drug Fact

Active ingredient

Benzocaine 15%

Purpose

Benzocaine for Pain Relief

Uses

temporary relief of pain and itching associated with insect bites, scrapes, minor cuts, minor burns, sunburn, or skin irritation

Warnings

For external use only. do not bandage.

Do not use. in the eyes or apply over large areas of the body, particularly over raw surfaces or blistered area - if product gets into the eyes. flush throughly with water and obtain medical attention. longer than one week unless directed by doctor.

Stop use and ask a doctor if. condition worsens or if symptoms persist for more than 7 days or clear up and occur again within a few days.

Keep out of reach of children

If swallowed, get medical help or contact a Poison Control Center right away.

Directions

♦ Do not use if label seal is broken prior to purchase. Keep swabs in original container when not in use.

♦ Hold the swab vertically, with the color band tip upwards. hold in the center of the stem with one hand and at the color band with the other.

♦ Bend the tip at the color band to one side until it snaps.

♦ Apply the product to the affected area.

♦ Discard swab after use.

Administration

For adult and children 2 and older. Apply directly onto affected area no more than 3 to 4 times daily.

Children under 2 years of age. Do not use, consult a doctor.

Other information

Avoid storing at excessive heat.

Inactive ingredients

Aloe Vera Gel. Ethoxydiglycol (diethylene glycol monoethyl ether), Glycerin, Menthol, PEG-8 (Polyethylene glycol 400), Propylene Glycol, Triclosan

Package Display Panel

Image of insect bite carton label